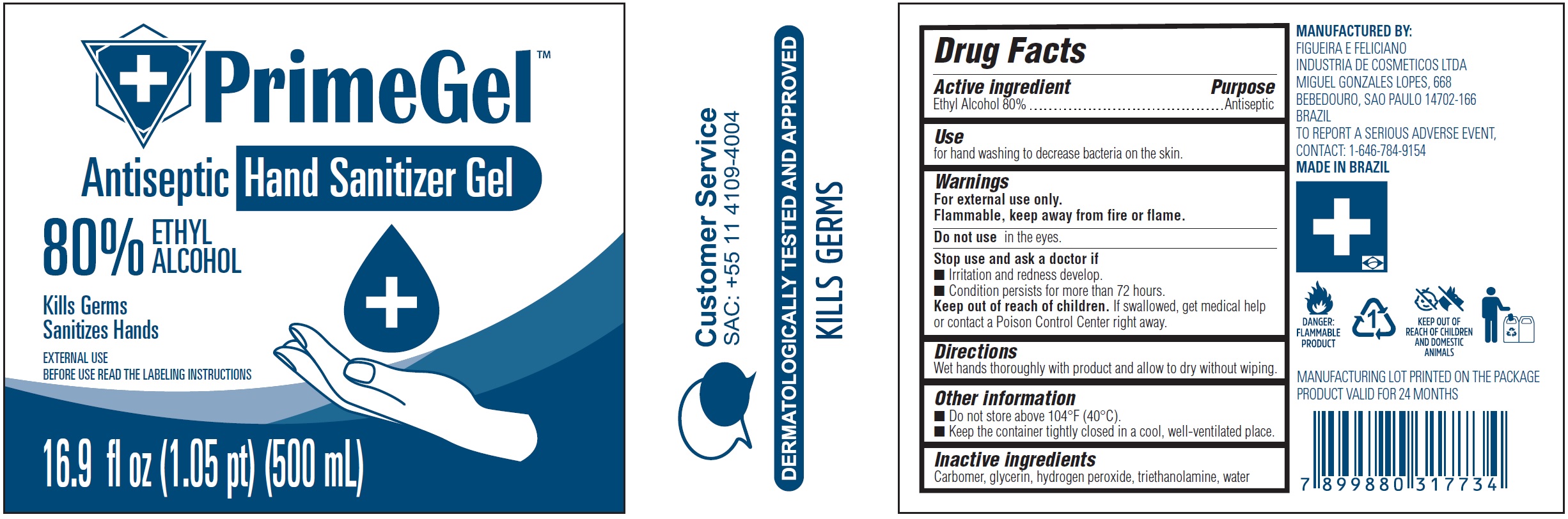 DRUG LABEL: PrimeGel Antiseptic Hand Sanitizer Gel 80 Ethyl Alcohol
NDC: 81717-001 | Form: GEL
Manufacturer: FIGUEIRA E FELICIANO INDUSTRIA DE COSMETICOS LTDA
Category: otc | Type: HUMAN OTC DRUG LABEL
Date: 20210518

ACTIVE INGREDIENTS: ALCOHOL 80 mL/100 mL
INACTIVE INGREDIENTS: CARBOMER HOMOPOLYMER, UNSPECIFIED TYPE; GLYCERIN; HYDROGEN PEROXIDE; TROLAMINE; WATER

PrimeGel Antiseptic Hand Sanitizer Gel 80% Ethyl Alcohol

Active ingredient

Ethyl Alcohol 80%

Purpose

Antiseptic

Use

for hand washing to decrease bacteria on the skin.

Warnings

For external use only.
Flammable, keep away from fire or flame.

Do not use

in the eyes.

Stop use and ask a doctor if

- Irritation and redness develop.
- Condition persists for more than 72 hours.

Keep out of reach of children.

If swallowed, get medical help or contact a Poison Control Center right away.

Directions

Wet hands thoroughly with product and allow to dry without wiping.

Other information

- Do not store above 104°F (40°C).
- Keep the container tightly closed in a cool, well-ventilated place.

Inactive ingredients

Carbomer, glycerin, hydrogen peroxide, triethanolamine, water